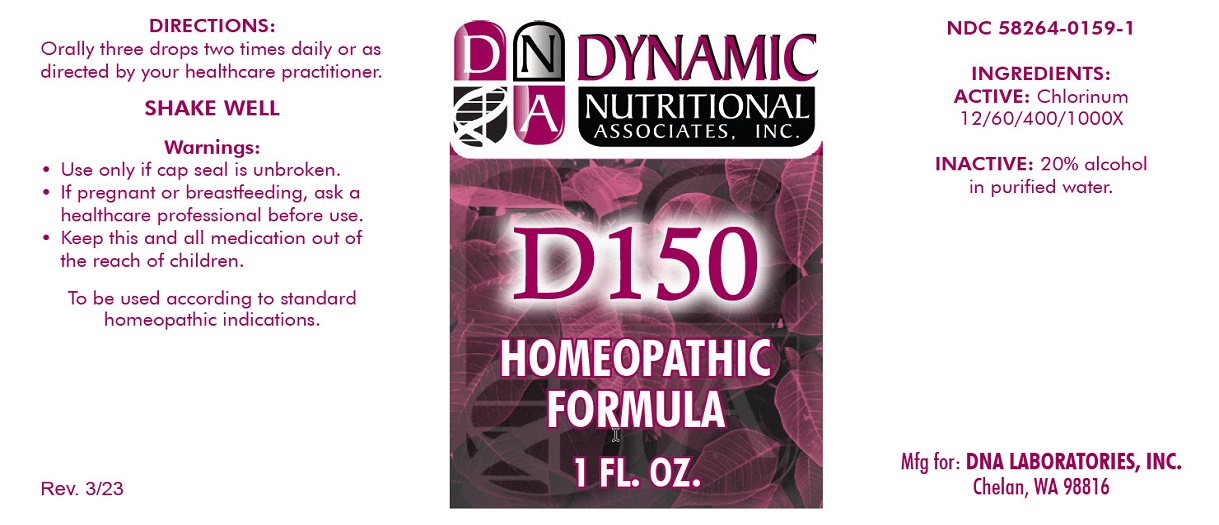 DRUG LABEL: D-150
NDC: 58264-0159 | Form: SOLUTION
Manufacturer: DNA Labs
Category: homeopathic | Type: HUMAN OTC DRUG LABEL
Date: 20250113

ACTIVE INGREDIENTS: CHLORINE 1000 [hp_X]/1 mL
INACTIVE INGREDIENTS: ALCOHOL; WATER

D-150

NDC 58264-0159-1

INGREDIENTS

ACTIVE

Chlorinum 12/60/400/1000X

INACTIVE

20% alcohol in purified water.

SUGGESTED DOSAGE

Orally three drops two times daily or as directed by your healthcare practitioner.

STORAGE AND HANDLING

SHAKE WELL

Warnings

- Use only if cap seal is unbroken.

PREGNANCY OR BREAST FEEDING

- If pregnant or breastfeeding, ask a healthcare professional before use.

KEEP OUT OF REACH OF CHILDREN

- Keep this and all medication out of the reach of children.

To be used according to standard homeopathic indications.

PRINCIPAL DISPLAY PANEL - 1 FL. OZ. Bottle Label

DYNAMIC

NUTRITIONAL

ASSOCIATES, INC.

D-150

HOMEOPATHIC

1 FL. OZ.